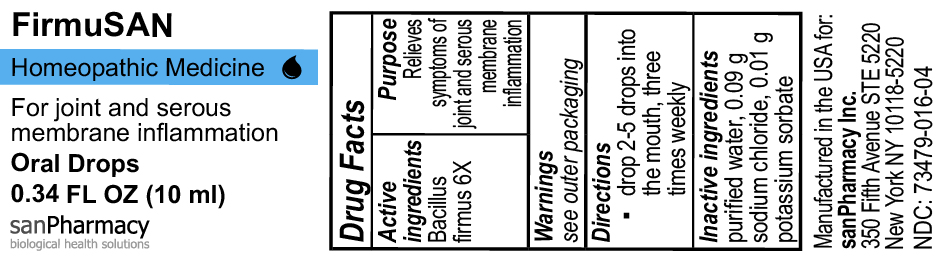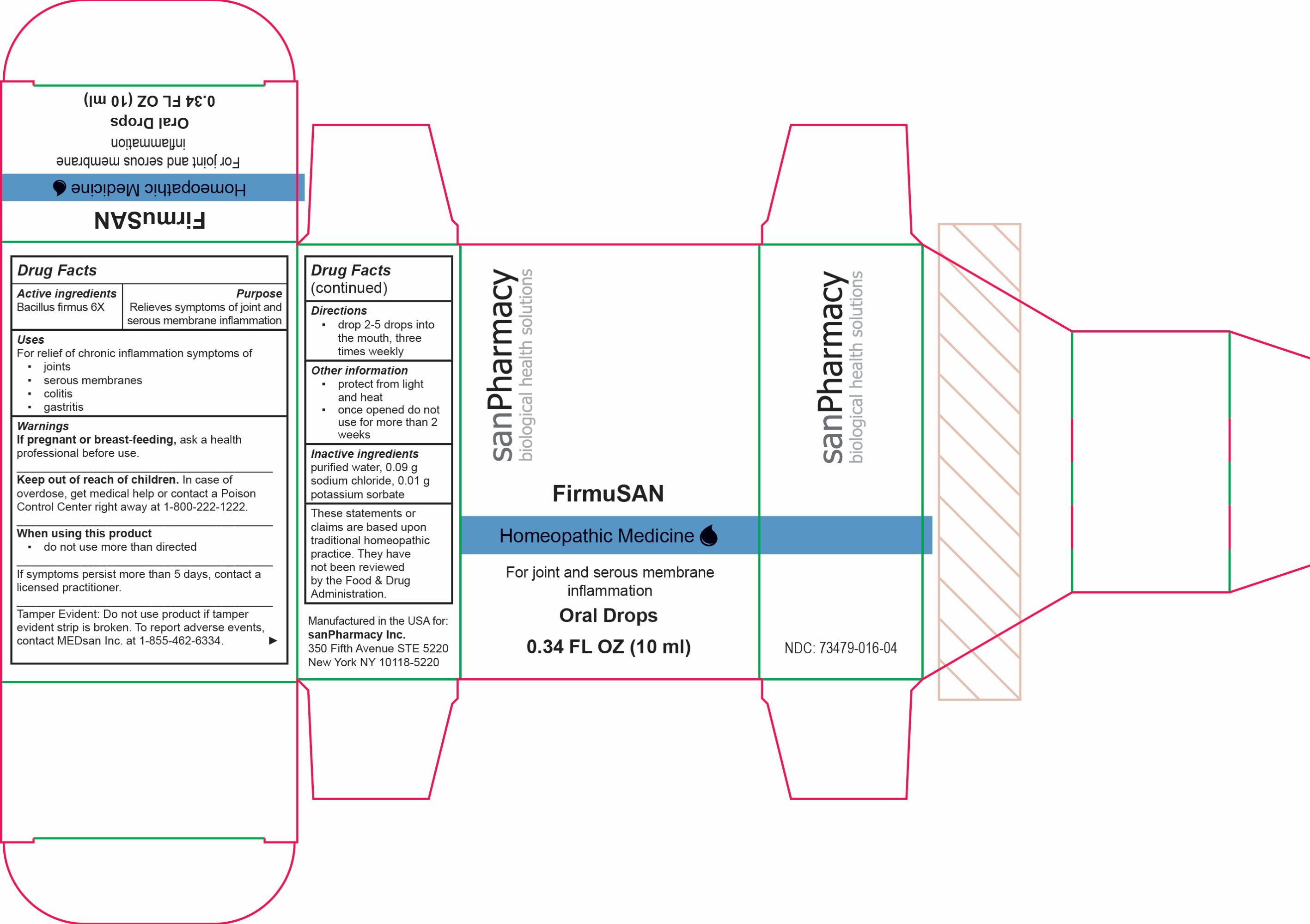 DRUG LABEL: FirmuSAN
NDC: 73479-016 | Form: SOLUTION/ DROPS
Manufacturer: sanPharmacy Inc.
Category: homeopathic | Type: HUMAN OTC DRUG LABEL
Date: 20240430

ACTIVE INGREDIENTS: BACILLUS FIRMUS 6 [hp_X]/10 mL
INACTIVE INGREDIENTS: SODIUM CHLORIDE 0.09 g/10 mL; WATER 10 mL/10 mL; POTASSIUM SORBATE 0.01 g/10 mL

FirmuSAN Drops

Indications

For joint and serous membrane inflammation

Purpose

Relieves symptoms of joint and serous membrane inflammation

Dosage

drop 2-5 drops into the mouth, three times weekly

Active ingredients

Bacillus firmus 6X

Inactive ingeredients

purified water, 0.09 g sodium chloride, 0.01 g potassium sorbate

Warnings

If pregnant or breast-feeding, ask a health professional before use.
______________________________
Keep out of reach of children. In case of overdose, get medical help or contact a Poison Control Center right away at 1-800-222-1222.
______________________________
When using this product
▪ do not use more than directed
______________________________
If symptoms persist more than 5 days, contact a licensed practitioner.
______________________________
Tamper Evident: Do not use product if tamper evident strip is broken. To report adverse events, contact MEDsan Inc. at 1-855-462-6334.

Keep out of reach of children. In case of overdose, get medical help or contact a Poison Control Center right away at 1-800-222-1222

Liability statement

These statements or claims are based upon traditional homeopathic practice. They have not been reviewed by the Food & Drug Administration

Manufactured in the USA for:
sanPharmacy Inc.
350 Fifth Avenue STE 5220
New York NY 10118-5220

STORAGE AND HANDLING

protect from light and heat▪once opened do not use for more than 2 weeks

PACKAGE LABEL

FirmuSAN

Homeopathic Medicine

For joint and serous membrane inflammation

Oral Drops

0.34 FL OZ (10 ml)

sanPharmacy

biological health solutions